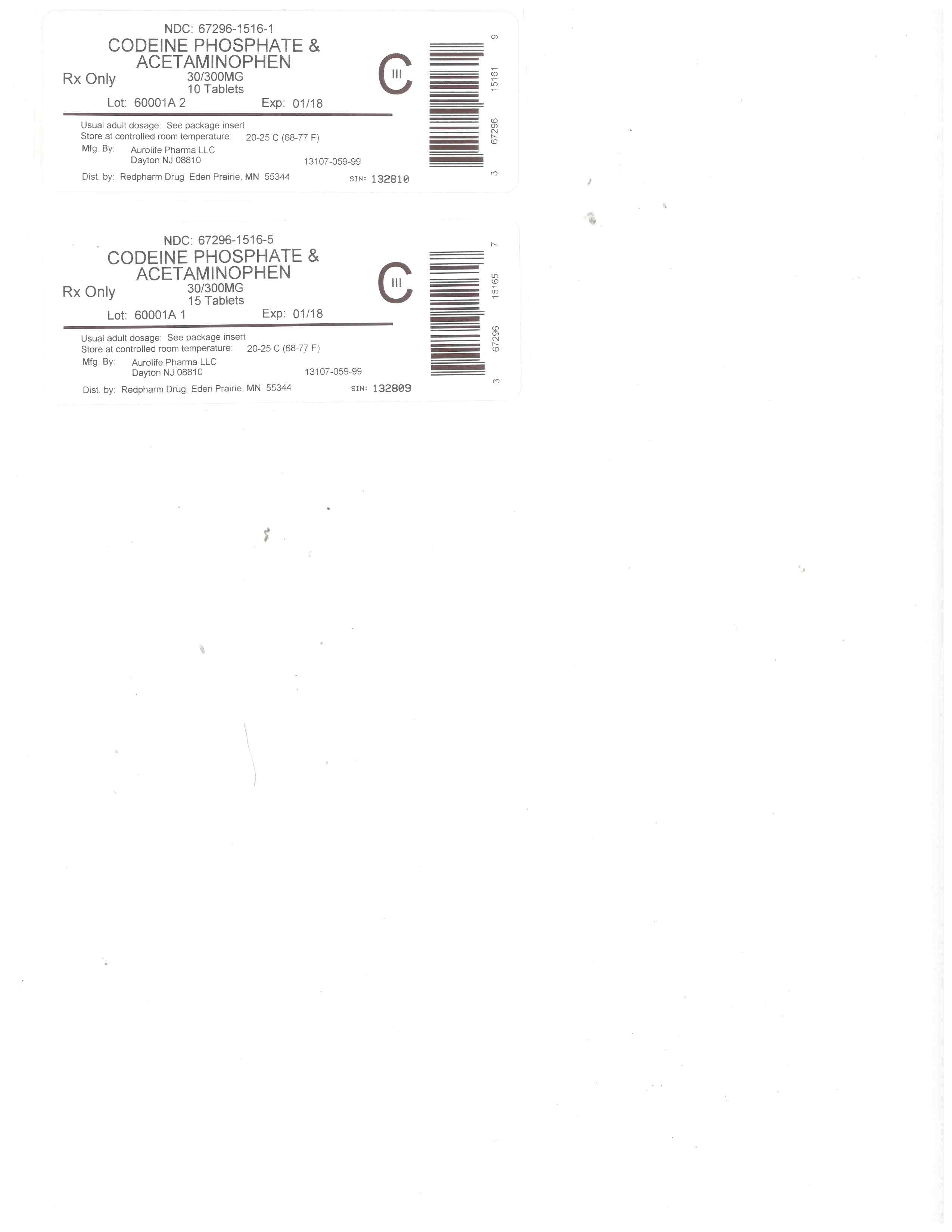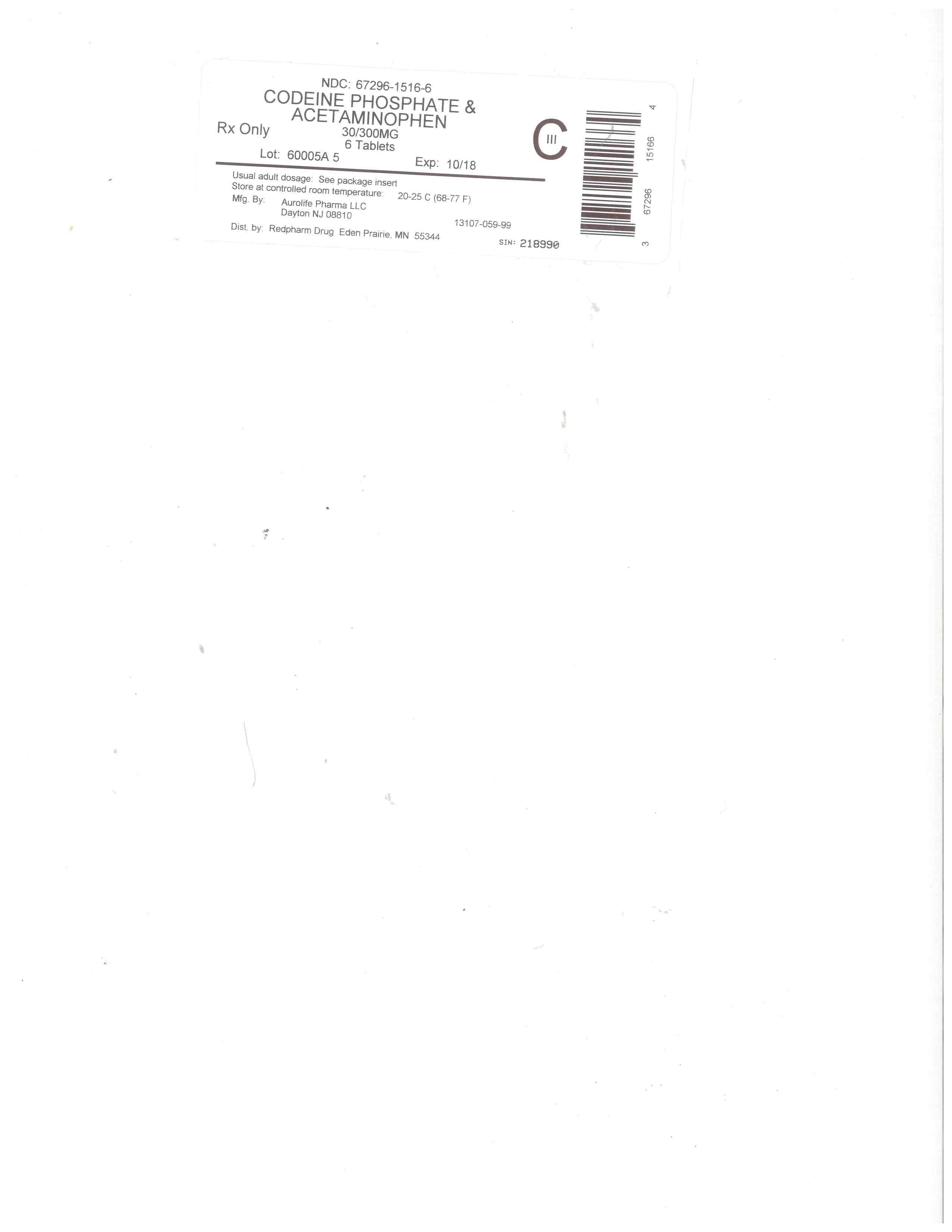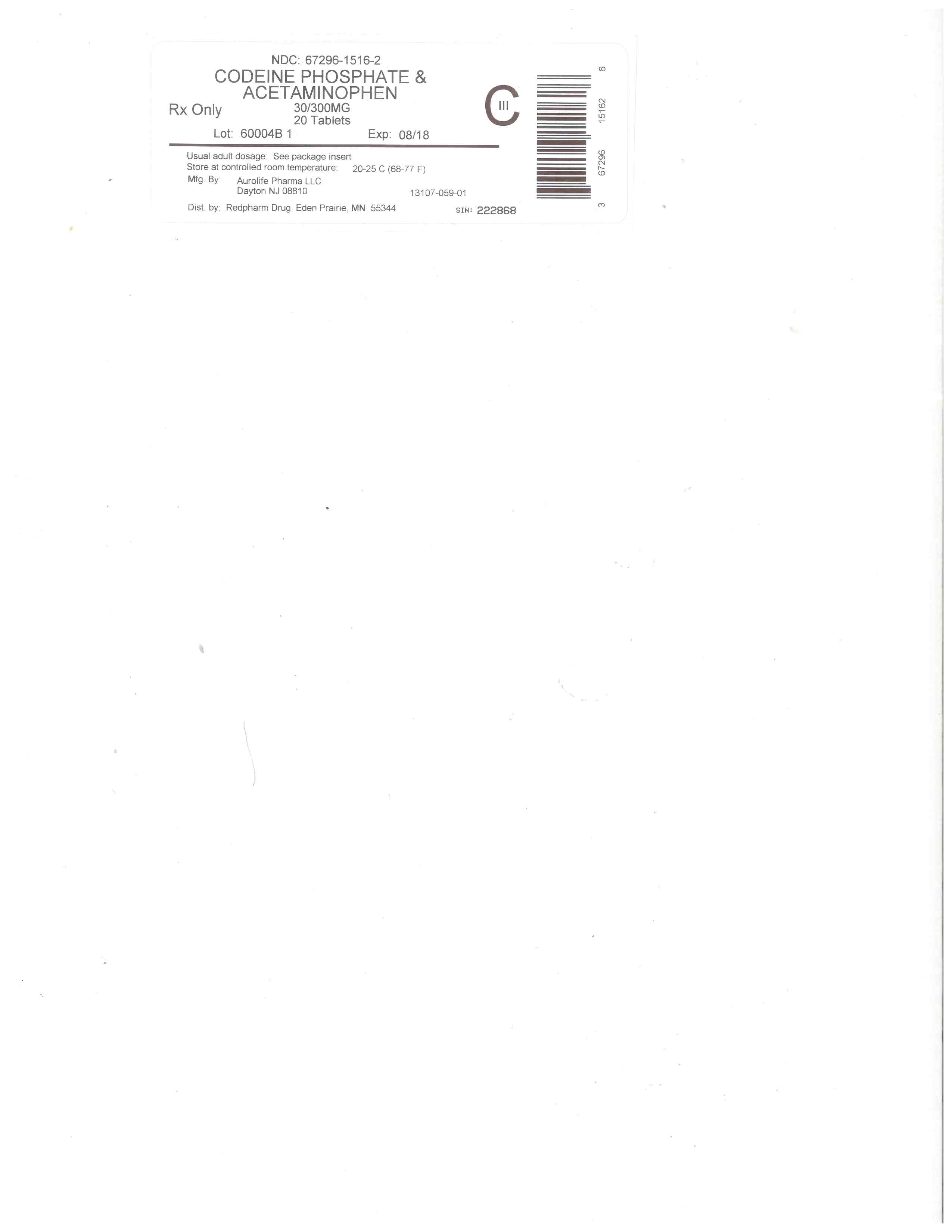 DRUG LABEL: Acetaminophen and Codeine Phosphate
NDC: 67296-1516 | Form: TABLET
Manufacturer: RedPharm Drug, Inc.
Category: prescription | Type: HUMAN PRESCRIPTION DRUG LABEL
Date: 20240808
DEA Schedule: CIII

ACTIVE INGREDIENTS: CODEINE PHOSPHATE 30 mg/1 1; ACETAMINOPHEN 300 mg/1 1
INACTIVE INGREDIENTS: MAGNESIUM STEARATE; CROSPOVIDONE (15 MPA.S AT 5%); SILICON DIOXIDE; CROSCARMELLOSE SODIUM; CELLULOSE, MICROCRYSTALLINE; POVIDONE; STARCH, CORN; SODIUM LAURYL SULFATE; STEARIC ACID

BOXED WARNING

WARNING: ADDICTION, ABUSE, AND MISUSE; LIFE-THREATENING RESPIRATORY DEPRESSION; ACCIDENTAL INGESTION; NEONATAL OPIOID WITHDRAWAL SYNDROME; DEATH RELATED TO ULTRA-RAPID METABOLISM OF CODEINE TO MORPHINE; HEPATOTOXICITY; CYTOCHROME P450 2D6 INTERACTION; and RISKS FROM CONCOMITANT USE WITH BENZODIAZEPINES OR OTHER CNS DEPRESSANTS
Addiction, Abuse, and Misuse
Acetaminophen and Codeine Phosphate Tablets expose patients and other users to the risks of opioid addiction, abuse and misuse, which can lead to overdose and death. Assess each patient’s risk prior to prescribing Acetaminophen and Codeine Phosphate Tablets, and monitor all patients regularly for the development of these behaviors and conditions [see WARNINGS].
Life-Threatening Respiratory Depression
Serious, life-threatening, or fatal respiratory depression may occur with use of acetaminophen and codeine phosphate tablets. Monitor for respiratory depression, especially during initiation of acetaminophen and codeine phosphate tablets or following a dose increase [see WARNINGS].
Accidental Ingestion
Accidental ingestion of even one dose of acetaminophen and codeine phosphate tablets, especially by children, can result in a fatal overdose of acetaminophen and codeine phosphate tablets [see WARNINGS].
Neonatal Opioid Withdrawal Syndrome
Prolonged use of acetaminophen and codeine phosphate tablets during pregnancy can result in neonatal opioid withdrawal syndrome, which may be life-threatening if not recognized and treated, and requires management according to protocols developed by neonatology experts. If opioid use is required for a prolonged period in a pregnant woman, advise the patient of the risk of neonatal opioid withdrawal syndrome and ensure that appropriate treatment will be available [see WARNINGS].

Death Related to Ultra-Rapid Metabolism of Codeine to Morphine
Respiratory depression and death have occurred in children who received codeine following tonsillectomy and/or adenoidectomy and had evidence of being ultra-rapid metabolizers of codeine due to a CYP2D6 polymorphism [see WARNINGS, PRECAUTIONS; Information for Patients/Caregivers, Nursing mothers].
Hepatotoxicity
Acetaminophen has been associated with cases of acute liver failure, at times resulting in liver transplant and death. Most of the cases of liver injury are associated with the use of acetaminophen at doses that exceed 4,000 milligrams per day, and often involve more than one acetaminophen-containing product [see WARNINGS].

Interactions with Drugs Affecting Cytochrome P450 Isoenzymes
The effects of concomitant use or discontinuation of cytochrome P450 3A4 inducers, 3A4 inhibitors, or 2D6 inhibitors with codeine are complex. Use of cytochrome P450 3A4 inducers, 3A4 inhibitors, or 2D6 inhibitors with Acetaminophen and Codeine Phosphate Tablets requires careful consideration of the effects on the parent drug, codeine, and the active metabolite, morphine.

Cytochrome P450 3A4 Interaction
The concomitant use of Acetaminophen and Codeine Phosphate Tablets with all cytochrome P450 3A4 inhibitors or discontinuation of a cytochrome P450 3A4 inducer may result in an increase in codeine plasma concentrations with subsequently greater metabolism by cytochrome P450 2D6, resulting in greater morphine levels, which could increase or prolong adverse reactions and may cause potentially fatal respiratory depression.

The concomitant use of Acetaminophen and Codeine Phosphate Tablets with all cytochrome P450 3A4 inducers or discontinuation of a cytochrome P450 3A4 inhibitor may result in lower codeine levels, greater norcodeine levels, and less metabolism via 2D6 with resultant lower morphine levels. This may be associated with a decrease in efficacy, and in some patients, may result in signs and symptoms of opioid withdrawal.

Follow patients receiving Acetaminophen and Codeine Phosphate Tablets and any CYP3A4 inhibitor or inducer for signs and symptoms that may reflect opioid toxicity and opioid withdrawal when Acetaminophen and Codeine Phosphate Tablets is used in conjunction with inhibitors and inducers of CYP3A4 [see Warnings, Precautions, Drug Interactions].

Cytochrome P450 2D6 Interaction
The concomitant use of Acetaminophen and Codeine Phosphate Tablets with all cytochrome P450 2D6 inhibitors may result in an increase in codeine plasma concentrations and a decrease in the plasma concentration of the active metabolite, morphine, which could result in an analgesic efficacy reduction or symptoms of opioid withdrawal.

The discontinuation of a cytochrome P450 2D6 inhibitor may result in a decrease in codeine plasma concentrations and an increase in the plasma concentration of the active metabolite, morphine, which could which could increase or prolong adverse reactions and may cause potentially fatal respiratory depression.

Follow patients receiving Acetaminophen and Codeine Phosphate Tablets and any CYP2D6 inhibitor for signs and symptoms that may reflect opioid toxicity and opioid withdrawal when Acetaminophen and Codeine Phosphate Tablets are used in conjunction with inhibitors of CYP2D6 [see WARNINGS,PRECAUTIONS, DRUG INTERACTIONS].

Risks from concomitant use with Benzodiazepines or other CNS Depressants
Concomitant use of opiods with benzodiazepines or other central nervous system (CNS) depressants including alcohol, may result in profound sedation, respiratory depression, coma, and death. [see WARNINGS,PRECAUTIONS; Drug interactions]
• Reserve concomitant prescribing of acetaminophen and codeine phosphate tablets and benzodiazepines or other CNS depressants for use in patients for whom alternative treatment options are inadequate.
• Limit dosages and durations to the minimum required.
• Follow patients for signs and symptoms of respiratory depression and sedation.

DESCRIPTION

Acetaminophen and codeine phosphate tablets, USP are for oral administration.
Acetaminophen, 4’-hydroxyacetanilide, a slightly bitter, white, odorless, crystalline powder, is a non-opiate, non-salicylate analgesic and antipyretic. It has the following structural formula:

[chemical structure]

Codeine phosphate, 7,8-didehydro-4,5α-epoxy-3-methoxy-17-methylmorphinan-6α-ol phosphate (1:1) (salt) hemihydrate, a white crystalline powder, is a narcotic analgesic and antitussive. It has the following structural formula:

[chemical structure]

Each tablet contains:
Acetaminophen............................300 mg
Codeine Phosphate........................15 mg
(Warning: May be habit forming)
OR
Acetaminophen............................300 mg
Codeine Phosphate........................30 mg
(Warning: May be habit forming)
OR
Acetaminophen............................300 mg
Codeine Phosphate........................60 mg
(Warning: May be habit forming)
In addition, each tablet contains the following inactive ingredients: colloidal silicon dioxide, croscarmellose sodium, crospovidone, magnesium stearate, microcrystalline cellulose, povidone, pregelatinized starch, sodium lauryl sulfate, and stearic acid.

CLINICAL PHARMACOLOGY

Mechanism of Action
Codeine is an opioid agonist relatively selective for the mu-opioid receptor, but with a much weaker affinity than morphine. The analgesic properties of codeine have been speculated to come from its conversion to morphine, although the exact mechanism of analgesic action remains unknown.
The precise mechanism of the analgesic properties of acetaminophen is not established but is thought to involve central actions.
Pharmacodynamics
Effects on the Central Nervous System
Codeine produces respiratory depression by direct action on brain stem respiratory centers. The respiratory depression involves a reduction in the responsiveness of the brain stem respiratory centers to both increases in carbon dioxide tension and electrical stimulation.
Codeine causes miosis, even in total darkness. Pinpoint pupils are a sign of opioid overdose but are not pathognomonic (e.g., pontine lesions of hemorrhagic or ischemic origins may produce similar findings). Marked mydriasis rather than miosis may be seen due to hypoxia in overdose situations.
Effects on the Gastrointestinal Tract and Other Smooth Muscle
Codeine causes a reduction in motility associated with an increase in smooth muscle tone in the antrum of the stomach and duodenum. Digestion of food in the small intestine is delayed and propulsive contractions are decreased. Propulsive peristaltic waves in the colon are decreased, while tone may be increased to the point of spasm, resulting in constipation. Other opioid-induced effects may include a reduction in biliary and pancreatic secretions, spasm of sphincter of Oddi, and transient elevations in serum amylase.
Effects on the Cardiovascular System
Codeine produces peripheral vasodilation which may result in orthostatic hypotension or syncope. Manifestations of histamine release and/or peripheral vasodilation may include pruritus, flushing, red eyes, sweating, and/or orthostatic hypotension.
Effects on the Endocrine System
Opioids inhibit the secretion of adrenocorticotropic hormone (ACTH), cortisol, and luteinizing hormone (LH) in humans [see Adverse Reactions]. They also stimulate prolactin, growth hormone (GH) secretion, and pancreatic secretion of insulin and glucagon.
Chronic use of opioids may influence the hypothalamic-pituitary-gonadal axis, leading to androgen deficiency that may manifest as low libido, impotence, erectile dysfunction, amenorrhea, or infertility. The causal role of opioids in the clinical syndrome of hypogonadism is unknown because the various medical, physical, lifestyle, and psychological stressors that may influence gonadal hormone levels have not been adequately controlled for in studies conducted to date [see Adverse Reactions].
Effects on the Immune System
Opioids have been shown to have a variety of effects on components of the immune system. The clinical significance of these findings is unknown. Overall, the effects of opioids appear to be modestly immunosuppressive.
Concentration–Efficacy Relationships
The minimum effective analgesic concentration will vary widely among patients, especially among patients who have been previously treated with potent agonist opioids. The minimum effective analgesic concentration of codeine for any individual patient may increase over time due to an increase in pain, the development of a new pain syndrome, and/or the development of analgesic tolerance [see Dosage and Administration].
Concentration–Adverse Reaction Relationships
There is a relationship between increasing codeine plasma concentration and increasing frequency of dose-related opioid adverse reactions such as nausea, vomiting, CNS effects, and respiratory depression. In opioid-tolerant patients, the situation may be altered by the development of tolerance to opioid-related adverse reactions see Dosage and Administration].
Pharmacokinetics
The behavior of the individual components is described below.
Codeine
Codeine is readily absorbed from the gastrointestinal tract. It is rapidly distributed from the intravascular spaces to the various body tissues, with preferential uptake by parenchymatous organs such as the liver, spleen and kidney. Codeine crosses the blood-brain barrier, and is found in fetal tissue and breast milk. The plasma concentration does not correlate with brain concentration or relief of pain; however, Codeine is about 7-25% bound to plasma proteins and does not accumulate in body tissues.
About 70 to 80% of the administered dose of codeine is metabolized by conjugation with glucuronic acid to codeine-6-glucuronide (C6G) and via O-demethylation to morphine (about 5 to 10%) and N-demethylation to norcodeine (about 10%) respectively. UDP-glucuronosyltransferase (UGT) 2B7 and 2B4 are the major enzymes mediating glucurodination of codeine to C6G. Cytochrome P450 2D6 is the major enzyme responsible for conversion of codeine to morphine and P450 3A4 is the major enzyme mediating conversion of codeine to norcodeine. Morphine and norcodeine are further metabolized by conjugation with glucuronic acid. The glucuronide metabolites of morphine are morphine-3-glucuronide (M3G) and morphine-6-glucuronide (M6G). Morphine and M6G are known to have analgesic activity in humans. The analgesic activity of C6G in humans is unknown. Norcodeine and M3G are generally not considered to possess analgesic properties.
The plasma half-life is about 2.9 hours. The elimination of codeine is primarily via the kidneys, and about 90% of an oral dose is excreted by the kidneys within 24 hours of dosing. The urinary secretion products consist of free and glucuronide conjugated codeine (about 70%), free and conjugated norcodeine (about 10%), free and conjugated morphine (about 10%), normorphine (4%), and hydrocodone (1%). The remainder of the dose is excreted in the feces.
At therapeutic doses, the analgesic effect reaches a peak within 2 hours and persists between 4 and 6 hours.
Acetaminophen
Acetaminophen is rapidly absorbed from the gastrointestinal tract and is distributed throughout most body tissues. A small fraction (10-25%) of acetaminophen is bound to plasma proteins.The plasma half-life is 1.25 to 3 hours, but may be increased by liver damage and following overdosage. Elimination of acetaminophen is principally by liver metabolism (conjugation) and subsequent renal excretion of metabolites. Acetaminophen is primarily metabolized in the liver by first-order kinetics and involves three principal separate pathways: conjugation with glucuronide; conjugation with sulfate; and oxidation via the cytochrome, P450-dependent, mixed-function oxidase enzyme pathway to form a reactive intermediate metabolite, which conjugates with glutathione and is then further metabolized to form cysteine and mercapturic acid conjugates. The principal cytochrome P450 isoenzyme involved appears to be CYP2E1, with CYP1A2 and CYP3A4 as additional pathways. Approximately 85% of an oral dose appears in the urine within 24 hours of administration, most as the glucuronide conjugate, with small amounts of other conjugates and unchanged drug.
See OVERDOSAGE for toxicity information.

INDICATIONS AND USAGE

Acetaminophen and codeine phosphate tablets are indicated for the management of mild to moderate pain,where treatment with an opioid is appropriate and for which alternative treatments are inadequate.

Limitations of Use

Because of the risks of addiction, abuse, and misuse, with opioids, even at recommended doses [see WARNINGS], reserve acetaminophen and codeine phosphate tablets for use in patients for whom alternative treatment options [e.g., non-opioid analgesics]

Have not provided adequate analgesia, or are not expected to provide adequate analgesia
Have not been tolerated, or are not expected to be tolerated

CONTRAINDICATIONS

Acetaminophen and codeine phosphate tablets are contraindicated in patients with:

Patients with significant respiratory depression [see WARNINGS].
Patients with acute or severe bronchial asthma in an unmonitored setting or in the absence of resuscitative equipment [see WARNINGS].
Postoperative pain management in children who have undergone tonsillectomy and/or adenoidectomy [see WARNINGS].
Patients with known or suspected gastrointestinal obstruction, including paralytic ileus [see WARNINGS].
Patients with hypersensitivity to codeine, acetaminophen, or any of the formulation excipients. (e.g., anaphylaxis) [see WARNINGS].
Concurrent use of monoamine oxidase inhibitors (MAOIs) or use of MAOIs within the last 14 days.

WARNINGS

Addiction, Abuse, and Misuse

An acetaminophen and codeine phosphate tablet contains codeine, a Schedule II controlled substance. As an opioid, acetaminophen and codeine phosphate tablets exposes users to the risks of addiction, abuse, and misuse [seeDRUG ABUSE AND DEPENDENCE].

Although the risk of addiction in any individual is unknown, it can occur in patients appropriately prescribed acetaminophen and codeine phosphate tablets. Addiction can occur at recommended dosages and if the drug is misused or abused.

Assess each patient’s risk for opioid addiction, abuse, or misuse prior to prescribing acetaminophen and codeine phosphate tablets, and monitor all patients receiving acetaminophen and codeine phosphate tablets for the development of these behaviors and conditions. Risks are increased in patients with a personal or family history of substance abuse (including drug or alcohol abuse or addiction) or mental illness (e.g., major depression). The potential for these risks should not, however, prevent the proper management of pain in any given patient. Patients at increased risk may be prescribed opioids such as acetaminophen and codeine phosphate tablets but use in such patients necessitates intensive counseling about the risks and misuse.

Opioids are sought by drug abusers and people with addiction disorders and are subject to criminal diversion. Consider these risks when prescribing or dispensing acetaminophen and codeine phosphate tablets. Strategies to reduce these risks include prescribing the drug in the smallest appropriate quantity and advising the patient on the proper disposal of unused drug [see PRECAUTIONS; Information for Patients]. Contact local state professional licensing board or state controlled substances authority for information on how to prevent and detect abuse or diversion of this product.

Life-Threatening Respiratory Depression

Serious, life-threatening, or fatal respiratory depression has been reported with the use of opioids, even when used as recommended. Respiratory depression, if not immediately recognized and treated, may lead to respiratory arrest and death. Management of respiratory depression may include close observation, supportive measures, and use of opioid antagonists, depending on the patient’s clinical status [seeOVERDOSAGE]. Carbon dioxide (CO2) retention from opioid-induced respiratory depression can exacerbate the sedating effects of opioids.

While serious, life-threatening, or fatal respiratory depression can occur at any time during the use of acetaminophen and codeine phosphate tablets the risk is greatest during the initiation of therapy or following a dosage increase. Monitor patients closely for respiratory depression, especially within the first 24 to 72 hours of initiating therapy with and following dosage increases of acetaminophen and codeine phosphate tablets.

To reduce the risk of respiratory depression, proper dosing and titration of acetaminophen and codeine phosphate tablets are essential [see DOSAGE AND ADMINISTRATION]. Overestimating the acetaminophen and codeine phosphate tablets dosage when converting patients from another opioid product can result in a fatal overdose with the first dose.

Accidental ingestion of acetaminophen and codeine phosphate tablets, especially by children, can result in respiratory depression and death due to an overdose of codeine.

Neonatal Opioid Withdrawal Syndrome

Prolonged use ofacetaminophen and codeine phosphate tabletsduring pregnancy can result in withdrawal in the neonate. Neonatal opioid withdrawal syndrome, unlike opioid withdrawal syndrome in adults, may be life-threatening if not recognized and treated, and requires management according to protocols developed by neonatology experts. Observe newborns for signs of neonatal opioid withdrawal syndrome and manage accordingly. Advise pregnant women using opioids for a prolonged period of the risk of neonatal opioid withdrawal syndrome and ensure that appropriate treatment will be available [see PRECAUTIONS, Information for Patients/Caregivers, Pregnancy].

Codeine Phosphate

Death Related to Ultra-Rapid Metabolism of Codeine to Morphine
Codeine-containing products are contraindicated for post-operative pain management in all pediatric patients undergoing tonsillectomy and/or adenoidectomy [see CONTRAINDICATIONS].
Respiratory depression and death have occurred in children who received codeine in the postoperative period following tonsillectomy and/or adenoidectomy and had evidence of being ultra-rapid metabolizers of codeine (i.e., multiple copies of the gene for cytochrome P450 isoenzyme 2D6 [CYP2D6] or high morphine concentrations). Deaths have also occurred in nursing infants who were exposed to high levels of morphine in breast milk because their mothers were ultra-rapid metabolizers of codeine [see PRECAUTIONS, Nursing Mothers]. Some individuals may be ultra-rapid metabolizers because of a specific CYP2D6 genotype (gene duplications denoted as *1/*1xN or *1/*2xN). The prevalence of this CYP2D6 phenotype varies widely and has been estimated at 0.5 to 1% in Chinese and Japanese, 0.5 to 1% in Hispanics, 1 to 10% in Caucasians, 3% in African Americans, and 16 to 28% in North Africans, Ethiopians, and Arabs. Data are not available for other ethnic groups. These individuals convert codeine into its active metabolite, morphine, more rapidly and completely than other people. This rapid conversion results in higher than expected serum morphine levels. Even at labeled dosage regimens, individuals who are ultra-rapid metabolizers may have life-threatening or fatal respiratory depression or experience signs of overdose (such as extreme sleepiness, confusion, or shallow breathing) [see OVERDOSAGE].
Children with obstructive sleep apnea who are treated with codeine for post-tonsillectomy and/or adenoidectomy pain may be particularly sensitive to the respiratory depressant effects of codeine that has been rapidly metabolized to morphine.
Risks of Interactions with Drugs Affecting Cytochrome P450 Isoenzymes
The effects of concomitant use or discontinuation of cytochrome P450 3A4 inducers, 3A4 inhibitors, or 2D6 inhibitors with codeine are complex. Use of cytochrome P450 3A4 inducers, 3A4 inhibitors, or 2D6 inhibitors with Acetaminophen and Codeine Phosphate Tablets requires careful consideration of the effects on the parent drug, codeine, and the active metabolite, morphine.
Cytochrome P450 3A4 Interaction
The concomitant use of Acetaminophen and Codeine Phosphate Tablets with all cytochrome P450 3A4 inhibitors , such as macrolide antibiotics (e.g., erythromycin), azole-antifungal agents (e.g., ketoconazole), and protease inhibitors (e.g., ritonavir) or discontinuation of a cytochrome P450 3A4 inducer such as rifampin, carbamazepine, and phenytoin, may result in an increase in codeine plasma concentrations with subsequently greater metabolism by cytochrome P450 2D6, resulting in greater morphine levels, which could increase or prolong adverse reactions and may cause potentially fatal respiratory depression.
The concomitant use of Acetaminophen and Codeine Phosphate Tablets with all cytochrome P450 3A4 inducers or discontinuation of a cytochrome P450 3A4 inhibitor may result in lower codeine levels, greater norcodeine levels, and less metabolism via 2D6 with resultant lower morphine levels. This may be associated with a decrease in efficacy, and in some patients, may result in signs and symptoms of opioid withdrawal.
Follow patients receiving Acetaminophen and Codeine Phosphate Tablets and any CYP3A4 inhibitor or inducer for signs and symptoms that may reflect opioid toxicity and opioid withdrawal when Acetaminophen and Codeine Phosphate Tablets are used in conjunction with inhibitors and inducers of CYP3A4 [see WARNINGS, PRECAUTIONS, Drug Interactions].
Risks of Concomitant Use or Discontinuation of Cytochrome P450 2D6 Inhibitors
The concomitant use of Acetaminophen and Codeine Phosphate Tablets with all cytochrome P450 2D6 inhibitors (e.g., amiodarone, quinidine) may result in an increase in codeine plasma concentrations and a decrease in active metabolite morphine plasma concentration which could result in an analgesic efficacy reduction or symptoms of opioid withdrawal.
Discontinuation of a concomitantly used cytochrome P450 2D6 inhibitor may result in a decrease in codeine plasma concentration and an increase in active metabolite morphine plasma concentration which could which could increase or prolong adverse reactions and may cause potentially fatal respiratory depression.
Follow patients receiving Acetaminophen and Codeine Phosphate Tablets and any CYP2D6 inhibitor for signs and symptoms that may reflect opioid toxicity and opioid withdrawal when Acetaminophen and Codeine Phosphate Tablets are used in conjunction with inhibitors of CYP2D6 [see PRECAUTIONS, Drug Interactions].
Risks from Concomitant Use with Benzodiazepines or Other CNS Depressants
Profound sedation, respiratory depression, coma, and death may result from the concomitant use of Acetaminophen and Codeine Phosphate Tablets with benzodiazepines or other CNS depressants (e.g., non-benzodiazepine sedatives/hypnotics, anxiolytics, tranquilizers, muscle relaxants, general anesthetics, antipsychotics, other opioids, alcohol). Because of these risks, reserve concomitant prescribing of these drugs for use in patients for whom alternative treatment options are inadequate.
Observational studies have demonstrated that concomitant use of opioid analgesics and benzodiazepines increases the risk of drug-related mortality compared to use of opioid analgesics alone. Because of similar pharmacological properties, it is reasonable to expect similar risk with the concomitant use of other CNS depressant drugs with opioid analgesics [see PRECAUTIONS, Drug Interactions].
If the decision is made to prescribe a benzodiazepine or other CNS depressant concomitantly with an opioid analgesic, prescribe the lowest effective dosages and minimum durations of concomitant use. In patients already receiving an opioid analgesic, prescribe a lower initial dose of the benzodiazepine or other CNS depressant than indicated in the absence of an opioid, and titrate based on clinical response. If an opioid analgesic is initiated in a patient already taking a benzodiazepine or other CNS depressant, prescribe a lower initial dose of the opioid analgesic, and titrate based on clinical response. Follow patients closely for signs and symptoms of respiratory depression and sedation.
Advise both patients and caregivers about the risks of respiratory depression and sedation when Acetaminophen and Codeine Phosphate Tablets are used with benzodiazepines or other CNS depressants (including alcohol and illicit drugs). Advise patients not to drive or operate heavy machinery until the effects of concomitant use of the benzodiazepine or other CNS depressant have been determined. Screen patients for risk of substance use disorders, including opioid abuse and misuse, and warn them of the risk for overdose and death associated with the use of additional CNS depressants including alcohol and illicit drugs [see PRECAUTIONS, Information for Patients, Drug Interactions].
Life-Threatening Respiratory Depression in Patients with Chronic Pulmonary Disease or Elderly, Cachectic, or Debilitated Patients
The use of Acetaminophen and Codeine Phosphate Tablets in patients with acute or severe bronchial asthma in an unmonitored setting or in the absence of resuscitative equipment is contraindicated.
Patients with Chronic Pulmonary Disease: Acetaminophen and Codeine Phosphate Tablets-treated patients with significant chronic obstructive pulmonary disease or cor pulmonale, and those with a substantially decreased respiratory reserve, hypoxia, hypercapnia, or pre-existing respiratory depression are at increased risk of decreased respiratory drive including apnea, even at recommended dosages of Acetaminophen and Codeine Phosphate Tablets [see WARNINGS; Life-Threatening Respiratory Depression].
Elderly, Cachectic, or Debilitated Patients: Life-threatening respiratory depression is more likely to occur in elderly, cachectic, or debilitated patients because they may have altered pharmacokinetics, including clearance, compared to younger, healthier patients [see WARNINGS; Respiratory Depression].
Monitor such patients closely, particularly when initiating and titrating Acetaminophen and Codeine Phosphate Tablets and when Acetaminophen and Codeine Phosphate Tablets is given concomitantly with other drugs that depress respiration [see WARNINGS; Life Threatening-Respiratory Depression]. Alternatively, consider the use of non-opioid analgesics in these patients.
Interaction with Monoamine Oxidase Inhibitors
Monoamine oxidase inhibitors (MAOIs) may potentiate the effects of morphine, codeine’s active metabolite including respiratory depression, coma, and confusion. Acetaminophen and Codeine Phosphate Tablets should not be used in patients taking MAOIs or within 14 days of stopping such treatment.
Adrenal Insufficiency
Cases of adrenal insufficiency have been reported with opioid use, more often following greater than 1 month of use. Presentation of adrenal insufficiency may include non-specific symptoms and signs including nausea, vomiting, anorexia, fatigue, weakness, dizziness, and low blood pressure. If adrenal insufficiency is suspected, confirm the diagnosis with diagnostic testing as soon as possible. If adrenal insufficiency is diagnosed, treat with physiologic replacement doses of corticosteroids. Wean the patient off of the opioid to allow adrenal function to recover and continue corticosteroid treatment until adrenal function recovers. Other opioids may be tried as some cases reported use of a different opioid without recurrence of adrenal insufficiency. The information available does not identify any particular opioids as being more likely to be associated with adrenal insufficiency.
Severe Hypotension
Acetaminophen and Codeine Phosphate Tablets may cause severe hypotension including hypotension and syncope in ambulatory patients. There is increased risk in patients whose ability to maintain blood pressure has already been compromised by a reduced blood volume or concurrent administration of certain CNS depressant drugs (e.g., phenothiazines or general anesthetics) [see PRECAUTIONS; Drug Interactions]. Monitor these patients for signs of hypotension after initiating or titrating the dosage of Acetaminophen and Codeine Phosphate Tablets. In patients with circulatory shock Acetaminophen and Codeine Phosphate Tablets may cause vasodilatation that can further reduce cardiac output and blood pressure. Avoid the use of Acetaminophen and Codeine Phosphate Tablets with circulatory shock.
Hepatotoxicity
Acetaminophen has been associated with cases of acute liver failure, at times resulting in liver transplant and death. Most of the cases of liver injury are associated with the use of acetaminophen at doses that exceed 4,000 milligrams per day, and often involve more than one acetaminophen-containing product. The excessive intake of acetaminophen may be intentional to cause self-harm or unintentional as patients attempt to obtain more pain relief or unknowingly take other acetaminophen-containing products.
The risk of acute liver failure is higher in individuals with underlying liver disease and in individuals who ingest alcohol while taking acetaminophen.
Instruct patients to look for acetaminophen or APAP on package labels and not to use more than one product that contains acetaminophen. Instruct patients to seek medical attention immediately upon ingestion of more than 4,000 milligrams of acetaminophen per day, even if they feel well.
Serious Skin Reactions
Rarely, acetaminophen may cause serious skin reactions such as acute generalized exanthematous pustulosis (AGEP), Stevens-Johnson Syndrome (SJS), and toxic epidermal necrolysis (TEN), which can be fatal. Patients should be informed about the signs of serious skin reactions, and use of the drug should be discontinued at the first appearance of skin rash or any other sign of hypersensitivity.
Hypersensitivity/Anaphylaxis
There have been postmarketing reports of hypersensitivity and anaphylaxis associated with use of acetaminophen. Clinical signs include swelling of the face, mouth, and throat, respiratory distress, urticaria, rash, pruritus, and vomiting. There were infrequent reports of life-threatening anaphylaxis requiring emergency medical attention. Instruct patients to discontinue acetaminophen and codeine phosphate tablets immediately and seek medical care if they experience these symptoms. Do not prescribe acetaminophen and codeine phosphate tablets for patients with acetaminophen allergy.
Risks of Use in Patients with Increased Intracranial Pressure, Brain Tumors, Head Injury, or Impaired Consciousness
In patients who may be susceptible to the intracranial effects of CO2 retention (e.g., those with evidence of increased intracranial pressure or brain tumors),
Acetaminophen and Codeine Phosphate Tablets may reduce respiratory drive, and the resultant CO2 retention can further increase intracranial pressure. Monitor such patients for signs of sedation and respiratory depression, particularly when initiating therapy with Acetaminophen and Codeine Phosphate Tablets.
Opioids may also obscure the clinical course in a patient with a head injury. Avoid the use of Acetaminophen and Codeine Phosphate Tablets in patients with impaired consciousness or coma.
Risks of Use in Patients with Gastrointestinal Conditions
Acetaminophen and Codeine Phosphate Tablets are contraindicated in patients with gastrointestinal obstruction, including paralytic ileus.
The administration of Acetaminophen and Codeine Phosphate Tablets or other opioids may obscure the diagnosis or clinical course in patients with acute abdominal conditions.
Acetaminophen and Codeine Phosphate Tablets may cause spasm of the sphincter of Oddi. Opioids may cause increases in serum amylase. Monitor patients with biliary tract disease, including acute pancreatitis, for worsening symptoms.
Sulfite Sensitivity
Acetaminophen and Codeine Phosphate Tablets contain sodium metabisulfite, a sulfite that may cause allergic-type reactions including anaphylactic symptoms and life-threatening or less severe asthmatic episodes in certain susceptible people. The overall prevalence of sulfite sensitivity in the general population is unknown and probably low. Sulfite sensitivity is seen more frequently in asthmatic than in nonasthmatic people.
Increased Risk of Seizures in Patients with Seizure Disorders
The codeine in Acetaminophen and Codeine Phosphate Tablets may increase the frequency of seizures in patients with seizure disorders, and may increase the risk of seizures occurring in other clinical settings associated with seizures. Monitor patients with a history of seizure disorders for worsened seizure control during Acetaminophen and Codeine Phosphate Tablets therapy.
Withdrawal
Avoid the use of mixed agonist/antagonist (e.g, pentazocine, nalbuphine, and butorphanol) or partial agonist (e.g., buprenorphine) analgesics in patients who are receiving a full opioid agonist analgesic, including Acetaminophen and Codeine Phosphate Tablets. In these patients, mixed agonist/antagonist and partial analgesics may reduce the analgesic effect and/or precipitate withdrawal symptoms.
When discontinuing Acetaminophen and Codeine Phosphate Tablets, gradually taper the dosage [see DOSAGE AND ADMINISTRATION]. Do not abruptly discontinue Acetaminophen and Codeine Phosphate Tablets [see DRUG ABUSE AND DEPENDENCE].

PRECAUTIONS

Risks of Driving and Operating Machinery

Acetaminophen and Codeine Phosphate Tablets may impair the mental or physical abilities needed to perform potentially hazardous activities such as driving a car or operating machinery. Warn patients not to drive or operate dangerous machinery unless they are tolerant to the effects of Acetaminophen and Codeine Phosphate Tablets and know how they will react to the medication [see PRECAUTIONS; Information for Patients/Caregivers].

Information for Patients/Caregivers

Addiction, Abuse, and Misuse

Inform patients that the use of acetaminophen and codeine phosphate tablets, even when taken as recommended, can result in addiction, abuse, and misuse, which can lead to overdose and death [see WARNINGS]. Instruct patients not to share acetaminophen and codeine phosphate tablets with others and to take steps to protect acetaminophen and codeine phosphate tabletsfrom theft or misuse.

Life-Threatening Respiratory Depression

Inform patients of the risk of life-threatening respiratory depression, including information that the risk is greatest when starting acetaminophen and codeine phosphate tablets or when the dosage is increased, and that it can occur even at recommended dosages [see WARNINGS]. Advise patients how to recognize respiratory depression and to seek medical attention if breathing difficulties develop.

Accidental Ingestion

Inform patients that accidental ingestion, especially by children, may result in respiratory depression or death [see WARNINGS]. Instruct patients to take steps to store acetaminophen and codeine phosphate tablets securely Advise patients to properly dispose of the Acetaminophen and Codeine Phosphate Tablets in accordance with local state guidelines and/or regulations.

Interactions with Benzodiazepines and Other CNS Depressants

Inform patients and caregivers that potentially fatal additive effects may occur if acetaminophen and codeine phosphate tablets is used with benzodiazepines or other CNS depressants,including alcohol, and not to use these concomitantly unless supervised by a health care provider [see WARNINGS, PRECAUTIONS; Drug Interactions].

Serotonin Syndrome

Inform patients that opioids could cause a rare but potentially life-threatening condition resulting from concomitant administration of serotonergic drugs. Warn patients of the symptoms of serotonin syndrome and to seek medical attention right away if symptoms develop.
Instruct patients to inform their healthcare provider if they are taking, or plan to take serotonergic medications [see PRECAUTIONS;Drug Interactions].
MAOI Interaction

Inform patients not to take Acetaminophen and Codeine Phosphate Tablets while using any drugs that inhibit monoamine oxidase. Patients should not start MAOIs while taking [TRADENAME] [see W&P or DI].

Adrenal Insufficiency

Inform patients that opioids could cause adrenal insufficiency, a potentially life-threatening condition. Adrenal insufficiency may present with non-specific symptoms and signs such as nausea, vomiting, anorexia, fatigue, weakness, dizziness, and low blood pressure. Advise patients to seek medical attention if they experience a constellation of these symptoms [see WARNINGS ].

Important Administration Instructions

Instruct patients how to properly take Acetaminophen and Codeine Phosphate Tablets [see DOSAGE AND ADMINISTRATION ].

Maximum Daily Dose of Acetaminophen

Inform patients not to take more than 4,000 milligrams of acetaminophen per day. Advise patients to call their healthcare provider if they have taken more than the recommended dose.

Hypotension

Inform patients that Acetaminophen and Codeine Phosphate Tablets may cause orthostatic hypotension and syncope. Instruct patients how to recognize symptoms of low blood pressure and how to reduce the risk of serious consequences should hypotension occur (e.g., sit or lie down, carefully rise from a sitting or lying position) [see WARNINGS; Hypotension].

Anaphylaxis

Inform patients that anaphylaxis has been reported with ingredients contained in Acetaminophen and Codeine Phosphate Oral Tablet. Advise patients how to recognize such a reaction, and if they develop signs of allergy such as a rash or difficulty breathing to stop taking Acetaminophen and Codeine Phosphate Oral Tablet and seek medical attention. [see CONTRAINDICATIONS, ADVERSE REACTIONS].

Pregnancy

Neonatal Opioid Withdrawal Syndrome

Inform female patients of reproductive potential that prolonged use of acetaminophen and codeine phosphate tablets during pregnancy can result in neonatal opioid withdrawal syndrome, which may be life-threatening if not recognized and treated [see WARNINGS, PRECAUTIONS; Pregnancy]

Embryo-Fetal Toxicity

Inform female patients of reproductive potential that acetaminophen and codeine phosphate tablets can cause fetal harm and to inform the prescriber of a known or suspected pregnancy [seePRECAUTIONS;Pregnancy].

Lactation

Advise patients that nursing mothers taking codeine can have higher morphine levels in their breast milk if they are ultra-rapid metabolizers. These higher levels of morphine in breast milk may lead to life-threatening or fatal side effects in nursing babies. Advise nursing mothers to watch for signs of morphine toxicity in their infants which includes increased sleepiness (more than usual), difficulty breastfeeding, breathing difficulties, or limpness. Instruct nursing mothers to talk to the baby’s doctor immediately if they notice these signs and, if they cannot reach the doctor right away, to take the baby to an emergency room or call 911 (or local emergency services) [see PRECAUTIONS; Nursing Mothers].

Infertility

Inform patients that chronic use of opioids may cause reduced fertility. It is not known whether these effects on fertility are reversible.

Driving or Operating Heavy Machinery

Inform patients that Acetaminophen and Codeine Phosphate Tablets may impair the mental and/or physical abilities required for the performance of potentially hazardous tasks such as driving a car or operating machinery and to avoid such tasks while taking this product, until they know how they will react to the medication.

Ultra-Rapid Metabolism of Codeine

Advise patients that some people have a genetic variation that results in codeine changing into morphine more rapidly and completely than other people. Most people are unaware of whether they are an ultra-rapid codeine metabolizer or not. These higher-than-normal levels of morphine in the blood may lead to life-threatening or fatal respiratory depression or signs of overdose such as extreme sleepiness, confusion, or shallow breathing. Children with this genetic variation who were prescribed codeine after tonsillectomy and/or adenoidectomy for obstructive sleep apnea may be at greatest risk based on reports of several deaths in this population due to respiratory depression. Codeine-containing products are contraindicated in all children who undergo tonsillectomy and/or adenoidectomy. Advise caregivers of children receiving codeine-containing products for other reasons to monitor for signs of respiratory depression.

Disposal of Unused Acetaminophen and Codeine Phosphate Tablets

1. Advise patients to properly dispose of the Acetaminophen and Codeine Phosphate Tablets Advise patients to throw the drug in the household trash following these steps. Remove them from their original containers and mix them with an undesirable substance, such as used coffee grounds or kitty litter (this makes the drug less appealing to children and pets, and unrecognizable to people who may intentionally go through the trash seeking drugs).

2. Place the mixture in a sealable bag, empty can, or other container to prevent the drug from leaking or breaking out of a garbage bag, or to dispose of in accordance with local state guidelines and/or regulations.

Drug Interactions

CYP2D6 Inhibitors

Codeine is metabolized by CYP2D6 to form morphine. The concomitant use of Acetaminophen and Codeine Phosphate Tablets and CYP2D6 inhibitors (e.g., paroxetine, fluoxetine, bupropion, quinidine) can increase the plasma concentration of codeine, but decreased the plasma concentration of active metabolite morphine, particularly when an inhibitor is added after a stable dose of Acetaminophen and Codeine Phosphate Tablet is achieved.

If concomitant use is necessary, consider dosage adjustment of Acetaminophen and Codeine Phosphate Tablets until stable drug effects are achieved.

After stopping a CYP2D6 inhibitor, as the effects of the inhibitor decline, the codeine plasma concentration will decrease but the morphine plasma concentration will increase. If a CYP2D6 inhibitor is discontinued, consider adjusting the Acetaminophen and Codeine Phosphate Tablets dosage until stable drug effects are achieved.

If concomitant use is necessary or if a CYP2D6 inhibitor is discontinued after concomitant use, monitor patients closely at frequent intervals. If signs and symptoms of respiratory depression or sedation occur, consider reducing the Acetaminophen and Codeine Phosphate Tablets dosage until stable drug effects are achieved.

CYP3A4 Inhibitors

The concomitant use of Acetaminophen and Codeine Phosphate Tablets and CYP3A4 inhibitors such as macrolide antibiotics (e.g., erythromycin), azole-antifungal agents (e.g. ketoconazole), and protease inhibitors (e.g., ritonavir), can increase the plasma concentration of codeine, resulting in increased or prolonged opioid effects, particularly when an inhibitor is added after a stable dose of Acetaminophen and Codeine Phosphate Tablets is achieved. If concomitant use is necessary, consider dosage reduction of Acetaminophen and Codeine Phosphate Tablets until stable drug effects are achieved. Monitor patients for respiratory depression and sedation at frequent intervals.

After stopping a CYP3A4 inhibitor, as the effects of the inhibitor decline, the codeine plasma concentration will decrease resulting in decreased opioid efficacy or a withdrawal syndrome in patients who had developed physical dependence to codeine. If a CYP3A4 inhibitor is discontinued, consider increasing the Acetaminophen and Codeine Phosphate Tablets dosage until stable drug effects are achieved. Monitor for signs of opioid withdrawal.

CYP3A4 Inducers

The concomitant use of Acetaminophen and Codeine Phosphate Tablets and CYP3A4 inducers (e.g., rifampin, carbamazepine, phenytoin) can decrease the plasma concentration of codeine, resulting in decreased efficacy or onset of a withdrawal syndrome in patients who have developed physical dependence to codeine. If concomitant use is necessary, consider increasing the Acetaminophen and Codeine Phosphate Tablets dosage until stable drug effects are achieved. Monitor for signs of opioid withdrawal.

After stopping a CYP3A4 inducer, as the effects of the inducer decline, the codeine plasma concentration will increase, which could increase or prolong both the therapeutic effects and adverse reactions, and may cause serious respiratory depression. If a CYP3A4 inducer is discontinued, consider Acetaminophen and Codeine Phosphate Tablets dosage reduction and monitor for signs of respiratory depression.

Benzodiazepines and other Central Nervous System (CNS) Depressants

Due to additive pharmacologic effect, the concomitant use of benzodiazepines or other CNS depressants such as alcohol, other sedatives/hypnotics, anxiolytics, tranquilizers, muscle

relaxants, general anesthetics, anti psychotics, and other opioids, can increases the risk of respiratory depression, profound sedation, coma, and death.

Reserve concomitant prescribing of these drugs for use in patients for whom alternative treatment options are inadequate. Limit dosages and durations to the minimum required. Follow patients closely for signs of respiratory depression and sedation [see WARNINGS].

Serotonergic Drugs

The concomitant use of opioids with other drugs that affect the serotonergic neurotransmitter system, such as selective serotonin reuptake inhibitors (SSRIs), serotonin and norepinephrine reuptake inhibitors (SNRIs), tricyclic antidepressants (TCAs), triptans, 5-HT3 receptor antagonists, drugs that effect the serotonin neurotransmitter system (e.g., mirtazapine, trazodone, tramadol), and monoamine oxidase (MAO) inhibitors (those intended to treat psychiatric disorders and also others, such as linezolid and intravenous methylene blue), has resulted in serotonin syndrome [see PRECAUTIONS ;Information for Patients].
If concomitant use is warranted, carefully observe the patient, particularly during treatment initiation and dose adjustment. Discontinue acetaminophen and codeine phosphate tablets if serotonin syndrome is suspected.

Monoamine Oxidase Inhibitors (MAOIs)
The concomitant use of opioids and MAOIs, such as phenelzine, tranylcypromine, linezolid, may manifest as serotonin syndrome or opioid toxicity. Advise patients taking Acetaminophen and Codeine Phosphate Tablets not to use MAOIs or within 14 days of stopping such treatment. If urgent use of an opioid is necessary, use test doses and frequent titration of small doses of other opioids (such as oxycodone, hydrocodone, oxymorphone, hydrocodone, or buprenorphine) to treat pain while closely monitoring blood pressure and signs and symptoms of CNS and respiratory depression.

Mixed Agonist/Antagonist and Partial Agonist Opioid Analgesics
The concomitant use of opioids with other opioid analgesics, such as butorphanol, nalbuphine, pentazocine, may reduce the analgesic effect of Acetaminophen and Codeine Phosphate Tablet and/or precipitate withdrawal symptoms.

Advise patient to avoid concomitant use of these drugs.

Muscle Relaxants
Acetaminophen and codeine tablet may enhance the neuromuscular blocking action of skeletal muscle relaxants and produce an increased degree of respiratory depression.If concomitant use is warranted, monitor patients for signs of respiratory depression that may be greater than otherwise expected and decrease the dosage of acetaminophen and codeine phosphate tablet and/or the muscle relaxant as necessary.

Diuretics
Opioids can reduce the efficacy of diuretics by inducing the release of antidiuretic hormone.
If concomitant use is warranted, monitor patients for signs of diminished diuresis and/or effects on blood pressure and increase the dosage of the diuretic as needed.

Anticholinergic Drugs
The concomitant use of anticholinergic drugs may increase risk of urinary retention and/or severe constipation, which may lead to paralytic ileus.
If concomitant use is warranted, monitor patients for signs of urinary retention or reduced gastric motility when Acetaminophen and Codeine Phosphate Tablet is used concomitantly with anticholinergic drugs.

Drug/Laboratory Test Interactions
Codeine may increase serum amylase levels.
Acetaminophen may produce false-positive test results for urinary 5-hydroxyindoleacetic acid.

Carcinogenesis, Mutagenesis, Impairment of Fertility
Carcinogenesis
Long-term studies to evaluate the carcinogenic potential of the combination of codeine and acetaminophen have not been conducted.
Two-year carcinogenicity studies have been conducted in F344/N rats and B6C3F1 mice. There was no evidence of carcinogenicity in male and female rats, respectively, at dietary doses up to 70 and 80 mg/kg/day of codeine sulfate (approximately 2 times the maximum recommended daily dose of 360 mg/day for adults on a mg/m2 basis) for two years. Similarly there was no evidence of carcinogenicity activity in male and female mice at dietary doses up to 400 mg/kg/day of codeine sulfate (approximately 5 times the maximum recommended daily dose of 360 mg/day for adults on a mg/m2 basis) for two years.
Long-term studies in mice and rats have been completed by the National Toxicology Program to evaluate the carcinogenic potential of acetaminophen. In 2-year feeding studies, F344/N rats and B6C3F1 mice were fed a diet containing acetaminophen up to 6000 ppm. Female rats demonstrated equivocal evidence of carcinogenic activity based on increased incidences of mononuclear cell leukemia at 0.8 times the maximum human daily dose (MHDD) of 4 grams/day, based on a body surface area comparison. In contrast, there was no evidence of carcinogenic activity in male rats that received up to 0.7 times or mice at up to 1.2-1.4 times the MHDD, based on a body surface area comparison.
Mutagenesis
Codeine sulfate was not mutagenic in the in vitro bacterial reverse mutation assay or clastogenic in the in vitro Chinese hamster ovary cell chromosome aberration assay.
In the published literature, acetaminophen has been reported to be clastogenic when administered at 1500 mg/kg/day to the rat model (3.6-times the MHDD, based on a body surface area comparison). In contrast, no clastogenicity was noted at a dose of 750 mg/kg/day (1.8-times the MHDD, based on a body surface area comparison), suggesting a threshold effect.
Impairment of Fertility
No nonclinical fertility studies have been conducted with codeine or the combination of codeine and acetaminophen.
In studies conducted by the National Toxicology Program, fertility assessments with acetaminophen have been completed in Swiss CD-1 mice via a continuous breeding study. There were no effects on fertility parameters in mice consuming up to 1.7 times the MHDD of acetaminophen, based on a body surface area comparison. Although there was no effect on sperm motility or sperm density in the epididymis, there was a significant increase in the percentage of abnormal sperm in mice consuming 1.78 times the MHDD (based on a body surface comparison) and there was a reduction in the number of mating pairs producing a fifth litter at this dose, suggesting the potential for cumulative toxicity with chronic administration of acetaminophen near the upper limit of daily dosing.
Published studies in rodents report that oral acetaminophen treatment of male animals at doses that are 1.2 times the MHDD and greater (based on a body surface comparison) result in decreased testicular weights, reduced spermatogenesis, reduced fertility, and reduced implantation sites in females given the same doses. These effects appear to increase with the duration of treatment. The clinical significance of these findings is not known.
Infertility

Chronic use of opioids may cause reduced fertility in females and males of reproductive potential. It is not known whether these effects on fertility are reversible [see ADVERSE REACTIONS].

Pregnancy

Teratogenic Effects: Pregnancy Category C
Codeine

A study in rats and rabbits reported no teratogenic effect of codeine administered during the period of organogenesis in doses ranging from 5 to 120 mg/kg. In the rat, doses at the 120 mg/kg level, in the toxic range for the adult animal, were associated with an increase in embryo resorption at the time of implantation. In another study a single 100 mg/kg subcutaneous dose of codeine administered to pregnant mice reportedly resulted in delayed ossification in the offspring.
There are no adequate and well-controlled studies in pregnant women. Acetaminophen and Codeine Phosphate Tablets should be used during pregnancy only if the potential benefit justifies the potential risk to the fetus.

Nonteratogenic Effects
Fetal/Neonatal Adverse Reactions

Prolonged use of opioid analgesics during pregnancy for medical or nonmedical purposes can result in physical dependence in the neonate and neonatal opioid withdrawal syndrome shortly after birth.
Neonatal opioid withdrawal syndrome presents as irritability, hyperactivity and abnormal sleep pattern, high pitched cry, tremor, vomiting, diarrhea and failure to gain weight. The onset, duration, and severity of neonatal opioid withdrawal syndrome vary based on the specific opioid used, duration of use, timing and amount of last maternal use, and rate of elimination of the drug by the newborn. Observe newborns for symptoms of neonatal opioid withdrawal syndrome and manage accordingly [see WARNINGS] .

Labor or Delivery

Opioids cross the placenta and may produce respiratory depression and psycho-physiologic effects in neonates. An opioid antagonist, such as naloxone, must be available for reversal of opioid-induced respiratory depression in the neonate. Acetaminophen and codeine phosphate tablets are not recommended for use in pregnant women during or immediately prior to labor, when other analgesic techniques are more appropriate. Opioid analgesics, including acetaminophen and codeine phosphate, can prolong labor through actions which temporarily reduce the strength, duration, and frequency of uterine contractions. However, this effect is not consistent and may be offset by an increased rate of cervical dilation, which tends to shorten labor. Monitor neonates exposed to opioid analgesics during labor for signs of excess sedation and respiratory depression.
Narcotic analgesics should be avoided during labor if delivery of a premature infant is anticipated. If the mother has received narcotic analgesics during labor, newborn infants should be observed closely for signs of respiratory depression. Resuscitation may be required [seeOVERDOSAGE ]. The effect of codeine, if any, on the later growth, development, and functional maturation of the child is unknown.

Nursing Mothers

Codeine is secreted into human milk. In women with normal codeine metabolism (normal CYP2D6 activity), the amount of codeine secreted into human milk is low and dose-dependent. However, some women are ultra-rapid metabolizers of codeine. These women achieve higher-than-expected serum levels of codeine’s active metabolite, morphine, leading to higher-than-expected levels of morphine in breast milk and potentially dangerously high serum morphine levels in their breastfed infants. Therefore, maternal use of codeine can potentially lead to serious adverse reactions, including death, in nursing infants.

The developmental and health benefits of breastfeeding should be considered along with the mother’s clinical need for Codeine Phosphate Tablets and any potential adverse effects on the breastfed infant from Codeine Phosphate Tablets or from the underlying maternal condition.

The risk of infant exposure to codeine and morphine through breast milk should be weighed against the benefits of breastfeeding for both the mother and baby. Caution should be exercised when codeine is administered to a nursing woman. If a codeine-containing product is selected, the lowest dose should be prescribed for the shortest period of time to achieve the desired clinical effect. Infants exposed to codeine phosphate through breast milk should be monitored for excess sedation and respiratory depression. Mothers using codeine should be informed about when to seek immediate medical care and how to identify the signs and symptoms of neonatal toxicity, such as drowsiness or sedation, difficulty breastfeeding, breathing difficulties, and decreased tone, in their baby. Nursing mothers who are ultra-rapid metabolizers may also experience overdose symptoms such as extreme sleepiness, confusion, or shallow breathing. Prescribers should closely monitor mother-infant pairs and notify treating pediatricians about the use of codeine during breastfeeding (See WARNINGS; Death Related to Ultra-Rapid Metabolism of Codeine to Morphine).

Acetaminophen is excreted in breast milk in small amounts, but the significance of its effect on nursing infants is not known. Because of the potential for serious adverse reactions in nursing infants from acetaminophen, a decision should be made whether to discontinue nursing or discontinue the drug, taking into account the importance of the drug to the mother.

Infants exposed to Acetaminophen and Codeine Tablets through breast milk should be monitored for excess sedation and respiratory depression. Withdrawal symptoms can occur in breastfed infants when maternal administration of an opioid analgesic is stopped, or when breast-feeding is stopped.

Pediatric Use

Respiratory depression and death have occurred in children with obstructive sleep apnea who received codeine in the post-operative period following tonsillectomy and/or adenoidectomy and had evidence of being ultra-rapid metabolizers of codeine (i.e., multiple copies of the gene for cytochrome P450 isoenzyme CYP2D6 or high morphine concentrations). These children may be particularly sensitive to the respiratory depressant effects of codeine that has been rapidly metabolized to morphine. Codeine-containing products are contraindicated for post-operative pain management in all pediatric patients undergoing tonsillectomy and/or adenoidectomy [seeCONTRAINDICATIONS, WARNINGS].

Geriatric Use

Elderly patients (aged 65 years or older) may have increased sensitivity to acetaminophen and codeine phosphate tablets. In general, use caution when selecting a dosage for an elderly patient, usually starting at the low end of the dosing range, reflecting the greater frequency of decreased hepatic, renal, or cardiac function and of concomitant disease or other drug therapy. Respiratory depression is the chief risk for elderly patients treated with opioids, and has occurred after large initial doses were administered to patients who were not opioid-tolerant or when opioids were co-administered with other agents that depress respiration. Titrate the dosage of acetaminophen and codeine phosphate tablets slowly in geriatric patients and monitor closely for signs of central nervous system and central nervous system depression [seeWARNINGS ].
These drugs are known to be substantially excreted by the kidney, and the risk of adverse reactions to this drug may be greater in patients with impaired renal function. Because elderly patients are more likely to have decreased renal function, care should be taken in dose selection, and it may be useful to monitor renal function.

ADVERSE REACTIONS

The following adverse reactions have been identified during post approval use of Acetaminophen and Codeine Phosphate Tablets. Because these reactions are reported voluntarily from a population of uncertain size, it is not always possible to reliably estimate their frequency or establish a causal relationship to drug exposure.
• Addiction, Abuse, and Misuse [see WARNINGS]
• Life-Threatening Respiratory Depression [see WARNINGS]
• Neonatal Opioid Withdrawal Syndrome [see WARNINGS]
• Ultra-rapid Metabolizers of Codeine [see WARNINGS]
• Interactions with CNS Depressants [see WARNINGS]
• Severe Hypotension [seeWARNINGS]
• Gastrointestinal Adverse Reactions [see WARNINGS]
• Seizures [see WARNINGS]
• Withdrawal [see WARNINGS]
Serious adverse reactions associated with codeine are respiratory depression and, to a lesser degree, circulatory depression, respiratory arrest, shock, and cardiac arrest.
The most frequently observed adverse reactions with codeine administration include drowsiness, lightheadedness, dizziness, sedation, shortness of breath, nausea, vomiting, sweating, and constipation.
Other adverse reactions include allergic reactions, euphoria, dysphoria, constipation, abdominal pain, pruritus, rash, thrombocytopenia, and agranulocytosis.
Cardiovascular system: faintness, flushing, hypotension, palpitations, syncope
Digestive System: abdominal cramps, anorexia, diarrhea, dry mouth, gastrointestinal distress, pancreatitis
Nervous system: anxiety, drowsiness, fatigue, headache, insomnia, nervousness, shakiness, somnolence, vertigo, visual disturbances, weakness
Skin and Appendages: rash, sweating, urticarial
• Serotonin syndrome: Cases of serotonin syndrome, a potentially life-threatening condition, have been reported during concomitant use of opioids with serotonergic drugs.
• Adrenal insufficiency: Cases of adrenal insufficiency have been reported with opioid use, more often following greater than one month of use.
• Anaphylaxis: Anaphylaxis has been reported with ingredients contained in Acetaminophen and Codeine Phosphate Tablets.
• Androgen deficiency: Cases of androgen deficiency have occurred with chronic use of opioids [see CLINICAL PHARMACOLOGY].

DRUG ABUSE AND DEPENDENCE

Controlled Substance

Acetaminophen and codeine phosphate tablet contains acetaminophen and codeine phosphate, a Schedule CII controlled substance.

Abuse

Acetaminophen and codeine phosphate tablet contains codeine, a substance with a high potential for abuse similar to other opioids including fentanyl, hydrocodone, hydrormorphone, methadone, morphine, oxycodone, oxymorphone, and tapentadol. Acetaminophen and Codeine Phosphate Tablets can be abused and is subject to misuse, addiction, and criminal diversion [see WARNINGS ].

All patients treated with opioids require careful monitoring for signs of abuse and addiction, since use of opioid analgesic products carries the risk of addiction even under appropriate medical use.

Prescription drug abuse is the intentional non-therapeutic use of a prescription drug, even once, for its rewarding psychological or physiological effects.

Drug addiction is a cluster of behavioral, cognitive, and physiological phenomena that develop after repeated substance use and includes: a strong desire to take the drug, difficulties in controlling its use, persisting in its use despite harmful,or potentially harmful,consequences, a higher priority given to drug use than to other activities and obligations, increased tolerance, and sometimes a physical withdrawal.

“Drug-seeking” behavior is very common in persons with substance use disorders. Drug-seeking tactics include emergency calls or visits near the end of office hours, refusal to undergo appropriate examination, testing, or referral, repeated “loss” of prescriptions, tampering with prescriptions and reluctance to provide prior medical records or contact information for other treating health care provider(s). “Doctor shopping” (visiting multiple prescribers) to obtain additional prescriptions is common among drug abusers and people suffering from untreated addiction. Preoccupation with achieving adequate pain relief can be appropriate behavior in a patient with poor pain control.

Abuse and addiction are separate and distinct from physical dependence and tolerance. Health care providers should be aware that addiction may not be accompanied by concurrent tolerance and symptoms of physical dependence in all addicts. In addition, abuse of opioids can occur in the absence of true addiction.

Acetaminophen and codeine phosphate tablets, like other opioids, can be diverted for non-medical use into illicit channels of distribution. Careful record-keeping of prescribing information, including quantity, frequency, and renewal requests, as required by state and federal law, is strongly advised. Proper assessment of the patient, proper prescribing practices, periodic re-evaluation of therapy, and proper dispensing and storage are appropriate measures that help to limit abuse of opioid drugs.

Risks Specific to Abuse of Acetaminophen and Codeine Phosphate Tablets

Acetaminophen and Codeine Phosphate Tablets is for oral use only. Abuse of Acetaminophen and Codeine Phosphate Tablets poses a risk of overdose and death. The risk is increased with concurrent use of Acetaminophen and Codeine Phosphate Tablets with alcohol and other central nervous system depressants.

Parenteral drug abuse is commonly associated with transmission of infectious diseases such as hepatitis and HIV.

Dependence

Both tolerance and physical dependence can develop during chronic opioid therapy. Tolerance is the need for increasing doses of opioids to maintain a defined effect such as analgesia (in the absence of disease progression or other external factors). Tolerance may occur to both the desired and undesired effects of drugs, and may develop at different rates for different effects. Physical dependence results in withdrawal symptoms after abrupt discontinuation or a significant dosage reduction of a drug. Withdrawal also may be precipitated through the administration of drugs with opioid antagonist activity (e.g., naloxone, nalmefene), mixed agonist/antagonist analgesics (pentazocine, butorphanol, nalbuphine), or partial agonists (buprenorphine). Physical dependence may not occur to a clinically significant degree until after several days to weeks of continued opioid usage.

Acetaminophen and codeine phosphate tablets should not be abruptly discontinued [see DOSAGE AND ADMINISTRATION]. If acetaminophen and codeine phosphate tablets are abruptly discontinued in a physically dependent patient, a withdrawal syndrome may occur. Some or all of the following can characterize this syndrome: restlessness, lacrimation, rhinorrhea, yawning, perspiration, chills, myalgia, and mydriasis. Other signs and symptoms also may develop, including: irritability, anxiety, backache, joint pain, weakness, abdominal cramps, insomnia, nausea, anorexia, vomiting, diarrhea, or increased blood pressure, respiratory rate, or heart rate. Infants born to mothers physically dependent on opioids will also be physically dependent and may exhibit respiratory difficulties and withdrawal signs [see PRECAUTIONS;Pregnancy].

OVERDOSAGE

Following an acute overdosage, toxicity may result from codeine or acetaminophen.
Clinical Presentation
Codeine
Acute overdosage with codeine can be manifested by respiratory depression, somnolence progressing to stupor or coma, skeletal muscle flaccidity, cold and clammy skin, constricted pupils, and, in some cases, pulmonary edema, bradycardia, hypotension, partial or complete airway obstruction, atypical snoring, and death. Marked mydriasis rather than miosis may be seen with hypoxia in overdose situations.
Acetaminophen
Dose-dependent, potentially fatal hepatic necrosis is the most serious adverse effect of acetminophen. Renal tubular necrosis, hypoglycemic coma, and coagulation defects may also occur.
Early symptoms following a potentially hepatotoxic overdose may include; anorexia, nausea, vomiting, diaphoresis, pallor and general malaise. Clinical and laboratory evidence of hepatic toxicity may not be apparent until 48 to 72 hours post-ingestion.
Treatment of Overdose

In case of overdose, priorities are the reestablishment of a patent and protected airway and institution of assisted or controlled ventilation, if needed. Employ other supportive measures (including oxygen and vasopressors) in the management of circulatory shock and pulmonary edema as indicated. Cardiac arrest or arrhythmias will require advanced life-support measures.

The opioid antagonists, naloxone or nalmefene, are specific antidotes to respiratory depression resulting from opioid overdose. For clinically significant respiratory or circulatory depression secondary to acetaminophen and codeine phosphate tablets overdose, administer an opioid antagonist. In patients who are physically dependent on any opioid agonist including Acetaminophen and Codeine Phosphate Tablets, an abrupt or complete reversal of opioid effects may precipitate an acute withdrawal syndrome. The severity of the withdrawal syndrome produced will depend on the degree of physical dependence and the dose of the antagonist administered. Please see the prescribing information for the specific opioid antagonist for details of their proper use.

Because the duration of opioid reversal is expected to be less than the duration of action of acetaminophen and codeine phosphate in acetaminophen and codeine phosphate tablets, carefully monitor the patient until spontaneous respiration is reliably re-established. If the response to an opioid antagonist is suboptimal or only brief in nature, administer additional antagonist as directed by the product’s prescribing information.

Acetaminophen

Gastric decontamination with activated charcoal should be administered just prior to N-acetylcysteine (NAC) to decrease systemic absorption if acetaminophen ingestion is known or suspected to have occurred within a few hours of presentation.

Serum acetaminophen levels should be obtained immediately if the patient presents 4 hours or more after ingestion to assess potential risk of hepatotoxicity; acetaminophen levels drawn less than 4 hours post-ingestion may be misleading. To obtain the best possible outcome, NAC should be administered as soon as possible where impending or evolving liver injury is suspected. Intravenous NAC may be administered when circumstances preclude oral administration.

Vigorous supportive therapy is required in severe intoxication. Procedures to limit the continuing absorption of the drug must be readily performed since the hepatic injury is dose-dependent and occurs early in the course of intoxication.

DOSAGE AND ADMINISTRATION

Use the lowest effective dosage for the shortest duration consistent with individual patient treatment goals [seeWARNINGS].
Important Dosage and Administration Instructions

Initiate the dosing regimen for each patient individually; taking into account the patient's severity of pain, patient response, prior analgesic treatment experience, and risk factors for addiction, abuse, and misuse [see WARNINGS].

Monitor patients closely for respiratory depression, especially within the first 24 to 72 hours of initiating therapy and following dosage increases with acetaminophen and codeine phosphate tablets and adjust the dosage accordingly [see WARNINGS].

Initial Dosage
Initiating Treatment with Acetaminophen and Codeine Phosphate Tablets
Dosage should be adjusted according to severity of pain and response of the patient. However, it should be kept in mind that tolerance to codeine can develop with continued use and that the incidence of untoward effects is dose related. Adult doses of codeine higher than 60 mg are associated with an increased incidence of adverse reactions and are not associated with greater efficacy.

The usual adult dosage is:

Acetaminophen and Codeine Phosphate Tablets (codeine 15 mg and acetaminophen 300 mg): Take 1 to 2 tablets every 4 hours as needed for pain.

Acetaminophen and Codeine Phosphate Tablets (codeine 30 mg and acetaminophen 300 mg): Take 1 to 2 tablets every 4 hours as needed for pain.

Acetaminophen and Codeine Phosphate Tablets (codeine 60 mg and acetaminophen 300 mg): Take one tablet every 4 hours as needed for pain.

Single Doses
(Range) Maximum
24-Hour Dose
Codeine Phosphate
15 mg to 60 mg
360 mg
Acetaminophen
300 mg to 1000 mg
4000 mg

The prescriber must determine the number of tablets per dose, and the maximum number of tablets per 24 hours, based upon the above dosage guidance. This information should be conveyed in the prescription.
The usual dose of codeine phosphate in children is 0.5 mg/kg. Doses may be repeated up to every 4 hours.

Conversion from Other Opioids to Acetaminophen and Codeine Phosphate Tablets
There is inter-patient variability in the potency of opioid drugs and opioid formulations. Therefore, a conservative approach is advised when determining the total daily dosage of Acetaminophen and Codeine Phosphate Tablets. It is safer to underestimate a patient’s 24-hour Acetaminophen and Codeine Phosphate Tablets dosage than to overestimate the 24-hour Acetaminophen and Codeine Phosphate Tablets dosage and manage an adverse reaction due to overdose.
Initiating Treatment with Acetaminophen and Codeine Phosphate Tablets

The prescriber must determine the number of tablets per dose, and the maximum number of tablets per 24 hours based upon the above dosage guidance. This information should be conveyed in the prescription.

It should be kept in mind, however, that tolerance to codeine can develop with continued use and that the incidence of untoward effects is dose related. Adult doses of codeine higher than 60 mg fail to give commensurate relief of pain but merely prolong analgesia and are associated with an appreciably increased incidence of undesirable side effects. Equivalently high doses in children would have similar effects.
Titration and Maintenance of Therapy

Individually titrate acetaminophen and codeine phosphate tablets to a dose that provides adequate analgesia and minimizes adverse reactions. Continually reevaluate patients receiving acetaminophen and codeine phosphate tablets to assess the maintenance of pain control and the relative incidence of adverse reactions, as well as monitoring for the development of addiction, abuse, or misuse [seeWARNINGS]. Frequent communication is important among the prescriber, other members of the healthcare team, the patient, and the caregiver/family during periods of changing analgesic requirements, including initial titration.

If the level of pain increases after dosage stabilization, attempt to identify the source of increased pain before increasing the acetaminophen and codeine phosphate tablets dosage. If unacceptable opioid-related adverse reactions are observed, consider reducing the dosage. Adjust the dosage to obtain an appropriate balance between management of pain and opioid-related adverse reactions.

Discontinuation of acetaminophen and codeine phosphate tablets

When a patient who has been taking acetaminophen and codeine phosphate tablets regularly and may be physically dependent no longer requires therapy with acetaminophen and codeine phosphate tablets,taper the dose gradually, by 25% to 50% every 2 to 4 days, while monitoring carefully for signs and symptoms of withdrawal. If the patient develops these signs or symptoms, raise the dose to the previous level and taper more slowly, either by increasing the interval between decreases, decreasing the amount of change in dose, or both. Do not abruptly discontinue Acetaminophen and Codeine Phosphate Tablets in a physically-dependent patient [see WARNINGS, DRUG ABUSE AND DEPENDENCE].

HOW SUPPLIED

Acetaminophen and codeine phosphate tablets, USP are supplied as follows:
300 mg/15 mg
White to off-white, round, flat-faced, beveled-edged tablets, debossed with “U35” on one side and plain on the other side.
Bottles of 30 NDC 13107-058-30
Bottles of 100 NDC 13107-058-01
Bottles of 500 NDC 13107-058-05
Bottles of 1000 NDC 13107-058-99
300 mg/30 mg
White to off-white, round, flat-faced, beveled-edged tablets, debossed with “U36” on one side and plain on the other side.
Bottles of 30 NDC 13107-059-30
Bottles of 100 NDC 13107-059-01
Bottles of 500 NDC 13107-059-05
Bottles of 1000 NDC 13107-059-99
300 mg/60 mg
White to off-white, round, flat-faced, beveled-edged tablets, debossed with “U37” on one side and plain on the other side.
Bottles of 30 NDC 13107-060-30
Bottles of 100 NDC 13107-060-01
Bottles of 500 NDC 13107-060-05
Bottles of 1000 NDC 13107-060-99
Store at 20° to 25°C (68° to 77°F). [See USP Controlled Room Temperature.]
Keep this and all medication out of the reach of children.
Protect from moisture. Dispense in a tight, light-resistant container as described in the USP.
PROTECT FROM LIGHT
Dispense with Medication Guide availableat www.aurobindousa.com/product-medication-guides
Manufactured by:
Aurolife Pharma LLC
Dayton, NJ 08810
Manufactured for:
Aurobindo Pharma USA, Inc.
Dayton, NJ 08810
Revised: 12/2016
LM 2126

MEDICATION GUIDE

Acetaminophenand Codeine Phosphate Tablets, USP CIII

ass-cet-ah-MEE-noe-fenwith KOE-deen FOSS-fate

Acetaminophen and Codeine PhosphateTablets are:

A strong prescription pain medicine that contains an opioid (narcotic) that is used to manage mild to moderate pain, when other pain treatments such as non-opioid pain medicines do not treat your pain well enough or you cannot tolerate them.
An opioid pain medicine that can put you at risk for overdose and death. Even if you take your dose correctly as prescribed you are at risk for opioid addiction, abuse, and misuse that can lead to death.

Important information about acetaminophen and codeinephosphate tablets:

Get emergency help right away if you take too much acetaminophen and codeine phosphate tablets (overdose). When you first start taking acetaminophen and codeine phosphate tablets, when your dose is changed, or if you take too much (overdose), serious or life-threatening breathing problems that can lead to death may occur.
Acetaminophen and Codeine Phosphate Tablets can cause severe drowsiness, breathing problems (respiratory depression), coma and death when taken with benzodiazepines or other medicines that depress consciousness.
Never give anyone else your acetaminophen and codeine phosphate tablets. They could die from taking it. Store acetaminophen and codeine phosphate tablets away from children and in a safe place to prevent stealing or abuse. Selling or giving away acetaminophen and codeine phosphate tablets are against the law.

Do not take Acetaminophen and Codeine Phosphate Tablets ifyou have:

•severe asthma, trouble breathing, or other lung problems.

•a bowel blockage or narrowing of the stomach or intestines.

•previously had an allergic reaction to codeine or acetaminophen.

Before taking acetaminophen and codeine phosphatetablets, tell your healthcare providerif you have a history of:

head injury, seizures
liver, kidney, thyroid problems
problems urinating
pancreas or gallbladder problems
abuse of street or prescription drugs, alcohol addiction, or mental health problems.

Tell your healthcare provider if you are:

pregnant or planning to become pregnant. Prolonged use of acetaminophen and codeine phosphate tablets during pregnancy can cause withdrawal symptoms in your newborn baby that could be life-threatening if not recognized and treated.
breastfeeding. acetaminophen and codeine phosphate passes into breast milk and may harm your baby.
taking prescription or over-the-counter medicines, vitamins, or herbal supplements. Taking acetaminophen and codeine phosphate tablets with certain other medicines can cause serious side effects that could lead to death.

When taking Acetaminophen and Codeine Phosphate Tablets:

•Do not change your dose. Take Acetaminophen and Codeine Phosphate Tablets exactly as prescribed by your healthcare provider. Use the lowest dose possible for the shortest time needed.

•Take your prescribed dose every 4 hours as needed. Do not take more than your prescribed dose. If you miss a dose, take your next dose when needed.

•Call your healthcare provider if the dose you are taking does not control your pain.

•If you have been taking Acetaminophen and Codeine Phosphate Tablets regularly, do not stop taking Acetaminophen and Codeine Phosphate Tablets without talking to your healthcare provider.

•After you stop taking Acetaminophen and Codeine Phosphate Tablets, to properly dispose of the Acetaminophen and Codeine Phosphate Tablets flush it down the toilet or dispose of in accordance with local state guidelines and/or regulations.

While taking acetaminophen and codeine phosphate tabletsDO NOT:

Drive or operate heavy machinery, until you know howacetaminophen and codeine phosphate tablets affects you. Acetaminophen and codeine phosphate tablets can make you sleepy, dizzy, or lightheaded.
Drink alcohol or use prescription or over-the-counter medicines that contain alcohol. Using products containing alcohol during treatment with acetaminophen and codeine phosphate tablets may cause you to overdose and die.

The possible side effects of acetaminophen and codeine phosphatetablets:

constipation, nausea, sleepiness, vomiting, tiredness, headache, dizziness, abdominal pain. Call your healthcare provider if you have any of these symptoms and they are severe.

Get emergency medical help if you have:

trouble breathing, shortness of breath, fast heartbeat, chest pain, swelling of your face, tongue, or throat, extreme drowsiness, light-headedness when changing positions, feeling faint, agitation, high body temperature, trouble walking, stiff muscles, or mental changes such as confusion.

These are not allthe possible side effects of acetaminophen and codeine phosphate tablets. Callyour doctor for medical advice about side effects. You may also request medicalinformation or to report suspected adverse reactions, contact Aurobindo PharmaUSA, Inc. at 1-866-850-2876 or FDA at 1-800-FDA-1088. For more information go todailymed.nlm.nih.gov

What are the ingredients in Acetaminophen and CodeinePhosphate Tablets?

Active Ingredients: acetaminophenand codeine phosphate

Inactive ingredients:colloidal silicon dioxide, croscarmellose sodium,crospovidone, magnesium stearate, microcrystalline cellulose, povidone,pregelatinized starch, sodium lauryl sulfate, and stearicacid

This Medication Guide has beenapproved by the U.S. Food and Drug Administration.

Manufacturedby:

Aurolife Pharma LLC

Dayton, NJ 08810

Manufacturedfor:

Aurobindo Pharma USA, Inc.

Dayton, NJ 08810

Revised: 12/2016